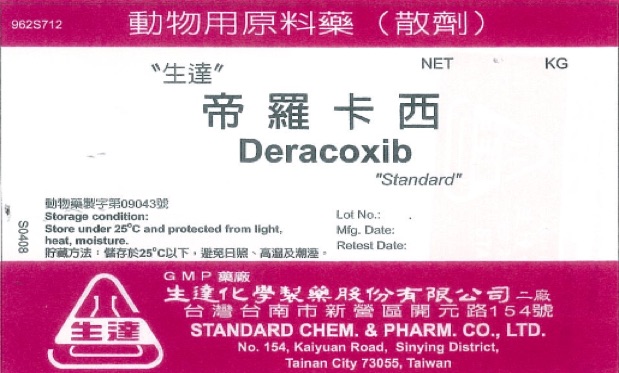 DRUG LABEL: NA
NDC: 63537-0071 | Form: POWDER
Manufacturer: Standard Chem. & Pharm. Co., Ltd.
Category: other | Type: BULK INGREDIENT
Date: 20211213

ACTIVE INGREDIENTS: DERACOXIB 1 kg/1 kg

Deracoxib